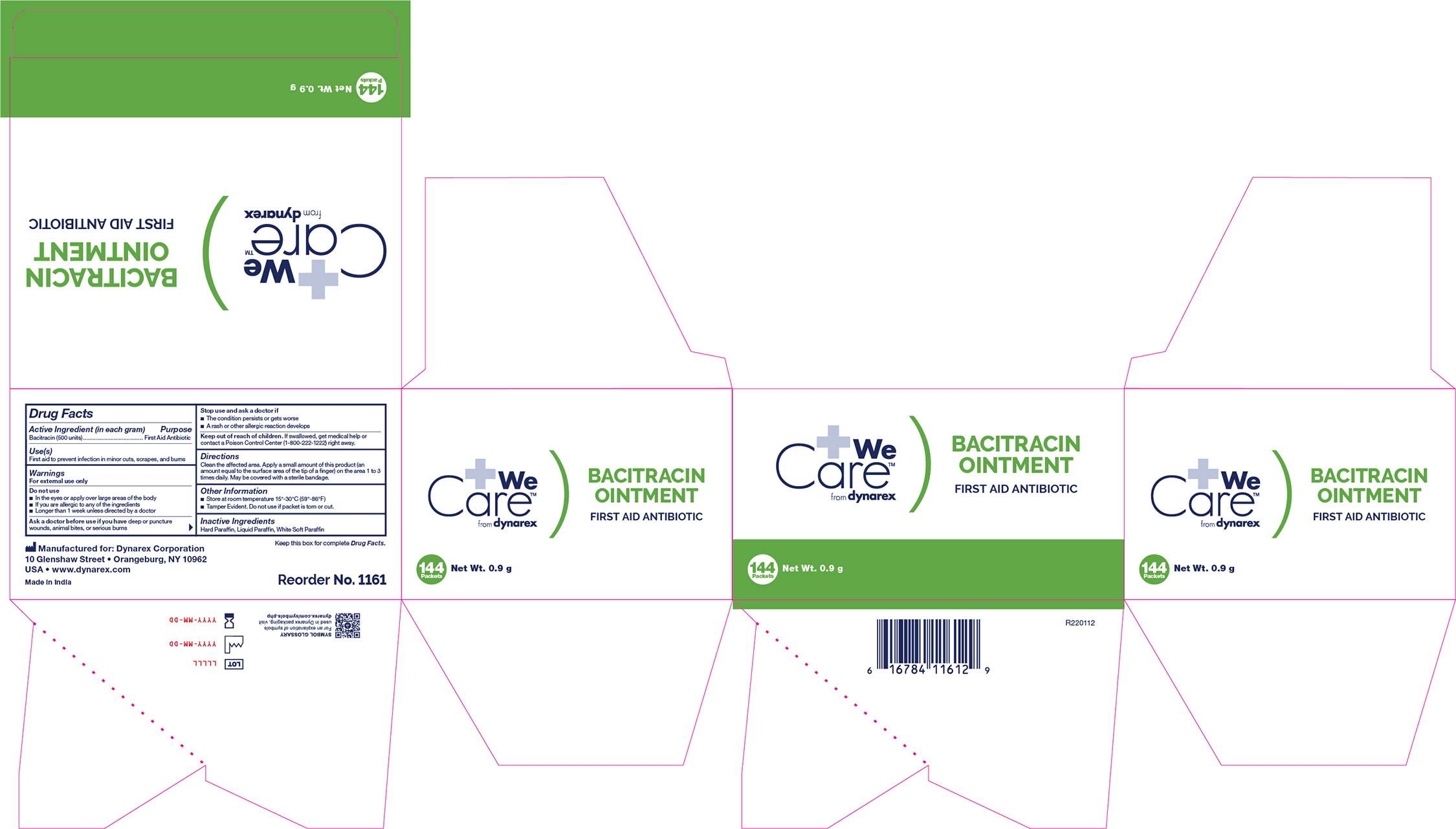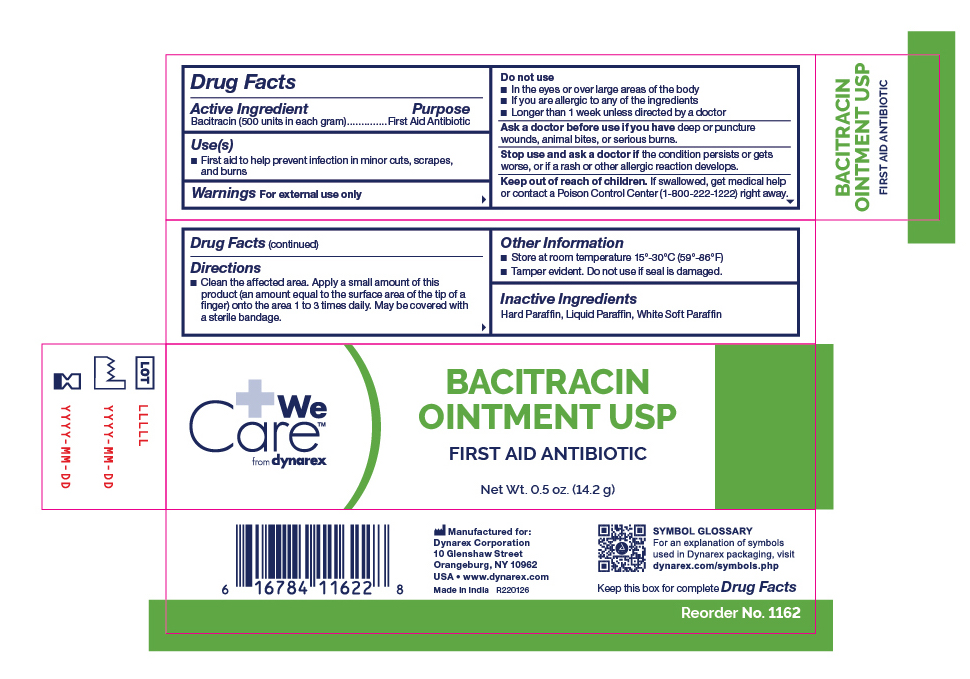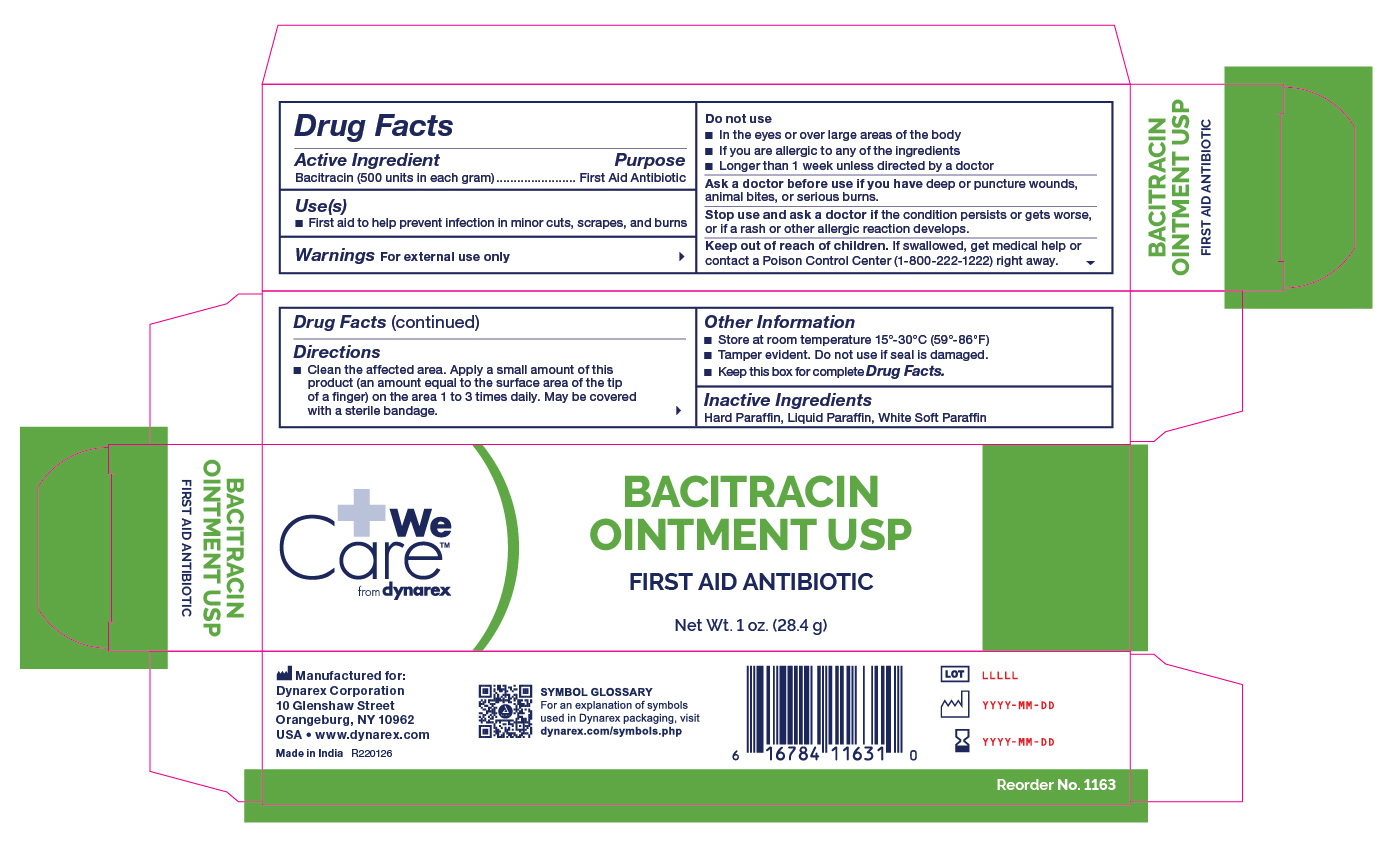 DRUG LABEL: Bacitracin
NDC: 67777-116 | Form: OINTMENT
Manufacturer: Dynarex Corporation
Category: otc | Type: HUMAN OTC DRUG LABEL
Date: 20241120

ACTIVE INGREDIENTS: BACITRACIN 500 [USP'U]/1000 mg
INACTIVE INGREDIENTS: WHITE PETROLATUM; PARAFFIN; MINERAL OIL

1161 Bacitracin NDC 67777-116-10
1162 Bacitracin NDC 67777-116-20
1163 Bacitracin NDC 67777-116-30

Active Ingredient

Bacitracin (500 units in each gram)

Purpose

First Aid Antibiotic

Use

First aid to help prevent infection in minor cuts, scrapes, and burns

Warnings

For External Use Only

Do not use

- In the eyes or apply over large areas of the body
- If you are allergic to any of the ingredients
- Longer than 1 week unless directed by a doctor

Ask a doctor before use if you have

deep or puncture wounds, animal bites, or serious burns

KEEP OUT OF REACH OF CHILDREN

If swallowed, get medical help or contact a Poison Control Center right away.

Directions

Clean the affected area. Apply a small amount of this product (an amount equal to the surface area of the tip of a finger) on the area 1 to 3 times daily. May be covered with a sterile bandage.

Other information

Store at room temperature

Inactive ingredients

Hard Paraffin, Liquid Paraffin, White Soft Paraffin

Label

1161 Bacitracin Ointment

Label

1162 Bacitracin Ointment

Label

1163 Bacitracin Ointment